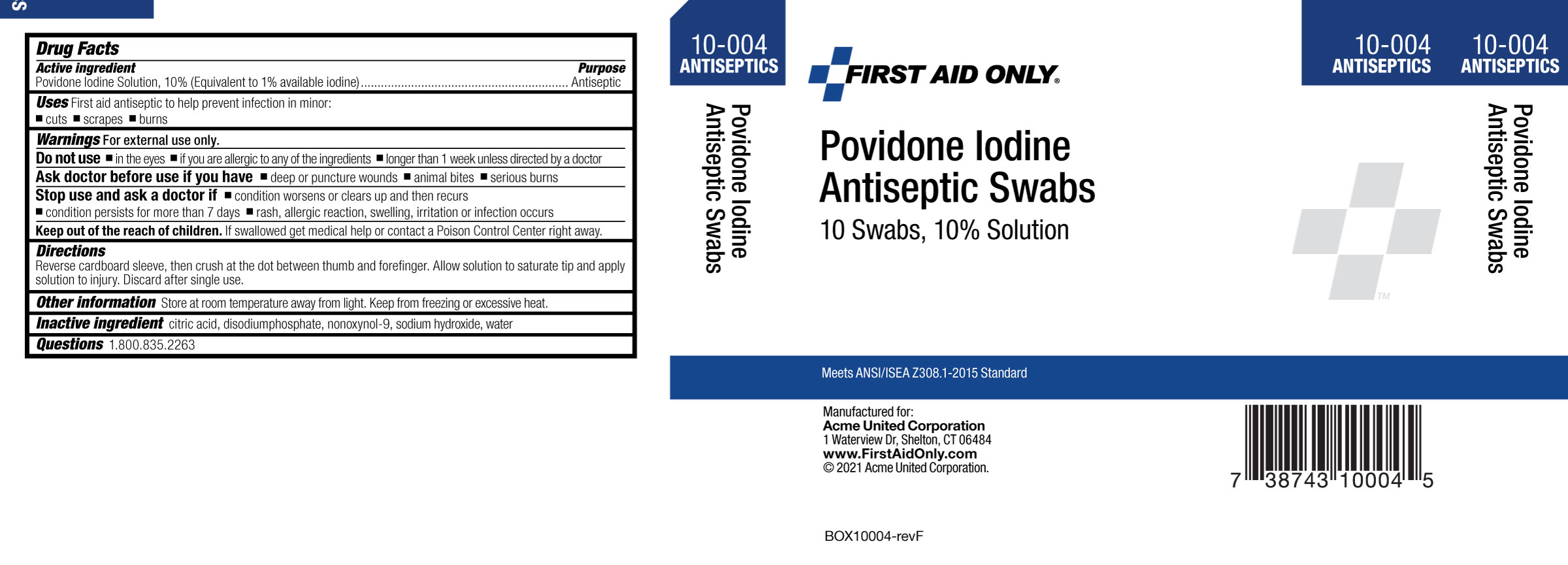 DRUG LABEL: POVIDONE-IODINE
NDC: 0924-5408 | Form: SOLUTION
Manufacturer: Acme United Corporation
Category: otc | Type: HUMAN OTC DRUG LABEL
Date: 20250617

ACTIVE INGREDIENTS: POVIDONE-IODINE 10 mg/1 mL
INACTIVE INGREDIENTS: CITRIC ACID MONOHYDRATE; SODIUM PHOSPHATE, DIBASIC, ANHYDROUS; NONOXYNOL-9; SODIUM HYDROXIDE; WATER

POVIDONE IODINE TOPICAL SOLUTION USP

Active Ingredients (each swab)

10% Povidone Iodine Solution USP, (1% available Iodine)

Purpose

Topical Antiseptic

Uses

First Aid Antiseptic To Help prevent infection in minor skin cuts and abrasions and burns.

Warnings

For external use only.

Do not use in the eyes; if you are allergic to any of the ingredients; longer than 1 week unless directed by a doctor.

Ask a doctor before use if you have• deep or puncture wounds • serious burns

Stop use and ask a doctor if • redness, irritation, swelling or pain persists or increases
• infection occurs.

Keep out of reach of children. If swallowed, get medical help immediately or contact a Poison Control Center right away.

Directions

Reverse cardboard sleeve then crush at dot between thumb and forefinger. Allow solution to saturate tip and apply solution to injury. Discard after single use.

Other Information

Store at room temperature away from light. Keep from freezing or excessive heat.

Inactive Ingredients

Citric acid, disodium phosphate, nonoxynol-9, sodium hydroxide, water.

Questions?

Call 1-800.835.2263

carton label